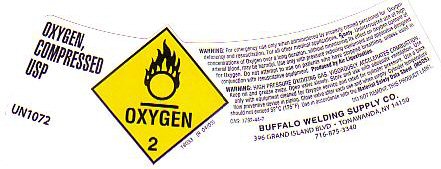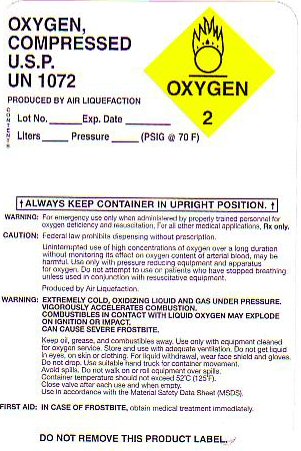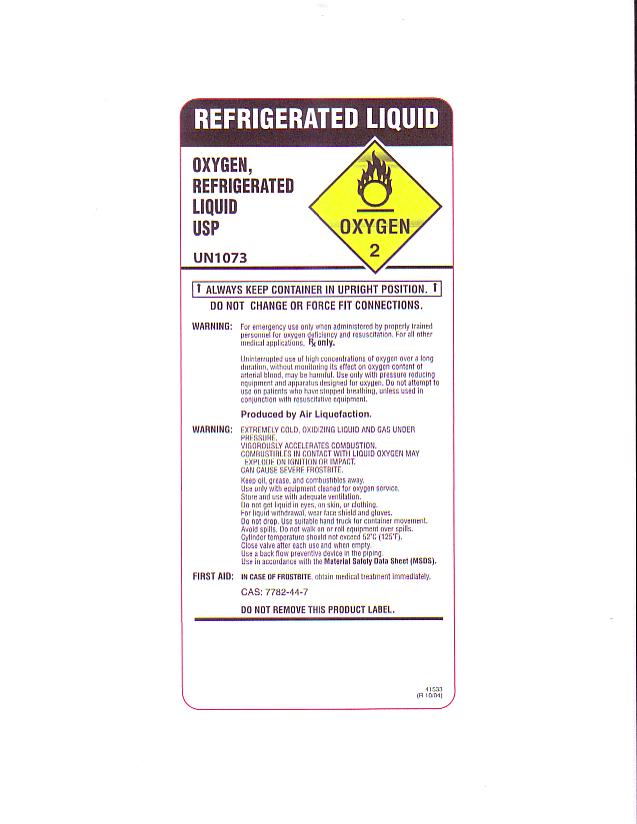 DRUG LABEL: OXYGEN
NDC: 25336-5563 | Form: GAS
Manufacturer: Buffalo Welding Corp
Category: prescription | Type: HUMAN PRESCRIPTION DRUG LABEL
Date: 20100101

ACTIVE INGREDIENTS: OXYGEN 99 L/100 L

OXYGEN COMPRESSED LABEL

OXYGEN COMPRESSED USP UN 1072 OXYGEN-2 PRODUCED BY AIR LIQUEFACTION. CAS 7782-44-7 18033 (R 04/05)

WARNING: HIGH PRESSURE GAS VIGOROUSLY ACCELERATES COMBUSTION.

OXYGEN COMPRESSED LABEL

OXYGEN COMPRESSED U.S.P. UN 1072 OXYGEN-2 PRODUCED BY AIR LIQUEFACTION

LOT NO ______ EXP DATE________ LITERS______ PRESSURE ______(PSIG AT 70F)

ALWAYS KEEP CONTAINER IN UPRIGHT POSITION.

WARNING: EXTREMELY COLD OXIDIZING LIQUID AND GAS UNDER PRESSURE. VIGOROUSLY ACCELERATES COMBUSTION. COMBUSTIBLES IN CONTACT WITH LIQUID OXYGEN MAY EXPLODE ON IGNITION OR IMPACT. CAN CAUSE SEVERE FROSTBITE

REFRIGERATED LIQUID LABEL

OXYGEN COMPRESSED U.S.P. UN 1072 OXYGEN-2 PRODUCED BY AIR LIQUEFACTION
ALWAYS KEEP CONTAINER IN UPRIGHT POSITION. DO NOT FORCE FIT OR CHANGE CONNECTIONS
WARNING: EXTREMELY COLD OXIDIZING LIQUID AND GAS UNDER PRESSURE. VIGOROUSLY ACCELERATES COMBUSTION. COMBUSTIBLES IN CONTACT WITH LIQUID OXYGEN MAY EXPLODE ON IGNITION OR IMPACT. CAN CAUSE SEVERE FROSTBITE

41533 (R 10/04) CAS 7782-44-7

PRODUCT WARNINGS AND PRECAUTIONS

FOR EMERGENCY USE ONLY WHEN ADMINISTERED BY PROPERLY TRAINED PERSONNEL FOR OXYGEN DEFICIENCY AND RESUSCITATION. FOR ALL OTHER MEDICAL APPLICATIONS Rx ONLY. FEDERAL LAW PROHIBITS DISPENSING WITHOUT A PRESCRIPTION. UNINTERRUPTED USE OF HIGH CONCENTRATIONS OF OXYGEN OVER A LONG DURATION WITHOUT MONITORING ITS EFFECT ON OXYGEN CONTENT OF ARTERIAL BLOOD MAY BE HARMFUL. USE ONLY WITH PRESSURE REDUCING EQUIPMENT AND APPARATUS FOR OXYGEN. DO NOT ATTEMPT TO USE ON PATIENTS WHO HAVE STOPPED BREATHING UNLESS USED IN CONJUNCTION WITH RESUSCITATIVE EQUIPMENT. PRODUCED BY AIR LIQUEFACTION.

WARNING: KEEP OIL GREASE AND COMBUSTIBLES AWAY. USE ONLY WITH EQUIPMENT CLEANED FOR OXYGEN SERVICE. STORE AND USE WITH ADEQUATE VENTILATION. DO NOT GET LIQUID IN EYES ON SKIN OR CLOTHING. FOR LIQUID WITHDRAWAL WEAR FACE SHIELD AND GLOVES. DO NOT DROP. USE SUITABLE HAND TRUCK FOR CONTAINER MOVEMENT. AVOID SPILLS. DO NOT WALK ON OR ROLL EQUIPMENT OVER SPILLS. CONTAINER TEMPERATURE SHOULD NOT EXCEED 52 c (125 f) CLOSE VALVE AFTER EACH USE AND WHEN EMPTY. USE IN ACCORDANCE WITH MATERIAL SAFETY DATA SHEET (MSDS)

FIRST AID: IN CASE OF FROSTBITE OBTAIN MEDICAL TREATMENT IMMEDIATELY.

DO NOT REMOVE THIS PRODUCT LABEL.